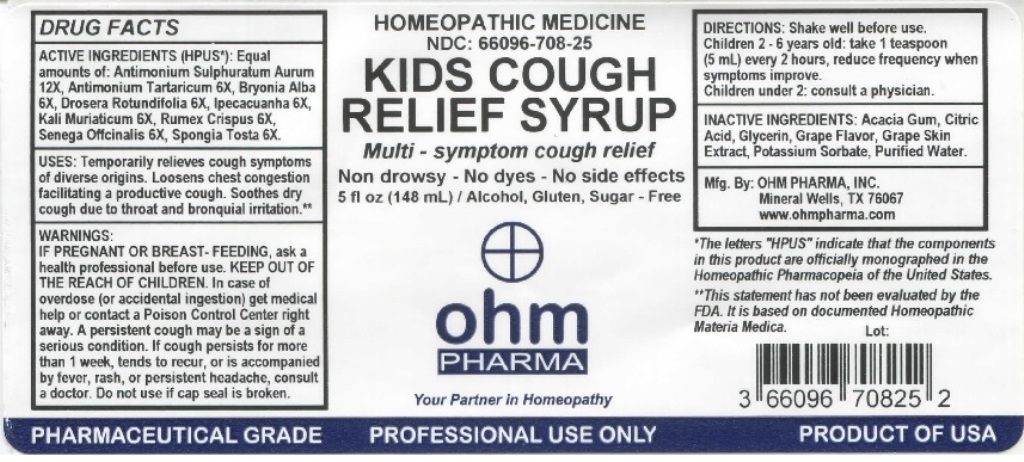 DRUG LABEL: Kids Cough Relief Syrup
NDC: 66096-708 | Form: LIQUID
Manufacturer: OHM PHARMA INC.
Category: homeopathic | Type: HUMAN OTC DRUG LABEL
Date: 20211229

ACTIVE INGREDIENTS: ANTIMONY PENTASULFIDE 12 [hp_X]/148 mL; ANTIMONY POTASSIUM TARTRATE 6 [hp_X]/148 mL; BRYONIA ALBA ROOT 6 [hp_X]/148 mL; DROSERA ROTUNDIFOLIA 6 [hp_X]/148 mL; IPECAC 6 [hp_X]/148 mL; POTASSIUM CHLORIDE 6 [hp_X]/148 mL; RUMEX CRISPUS ROOT 6 [hp_X]/148 mL; POLYGALA SENEGA ROOT 6 [hp_X]/148 mL; SPONGIA OFFICINALIS SKELETON, ROASTED 6 [hp_X]/148 mL
INACTIVE INGREDIENTS: ACACIA; CITRIC ACID MONOHYDRATE; GLYCERIN; WINE GRAPE; VITIS VINIFERA ANTHOCYANINS; POTASSIUM SORBATE; WATER

OHM Kids Cough Relief Syrup

ACTIVE INGREDIENT

ACTIVE INGREDIENTS (HPUS*): Equal amounts of: Antimonium Sulphuratum Aureum 12X, Antimonium Tartaricum 6X, Bryonia Alba 6X, Drosera Rotundifolia 6X, Ipecacuanha 6X, Kali Muriaticum 6X, Rumex Crispus 6X, Senega Officinalis 6X, Spongia Tosta 6X.

*The letters "HPUS" indicate that the components in the product are officially monographed in the Homeopathic Pharmacopeia of the United States.

INDICATIONS AND USAGE

USES: Temporarily relieves cough symptoms of diverse origins. Loosens chest congestion facilitating a productive cough. Soothes dry cough due to throat and bronquial irritation.**

**This statement has not been evaluated by the FDA. It is based on documented Homeopathic Materia Medica.

WARNINGS

WARNINGS: IF PREGNANT OR BREAST-FEEDING, ask a health care professional before use. In case of overdose (or accidental ingestion) get medical help or contact a Poison Control Center right away. A persistent cough may be a sign of a serious condition. If cough persists for more than 1 week, tends to recur, or is accompanied by fever, rash, or persistent headache, consult a doctor.

- KEEP OUT OF REACH OF CHILDREN.

DOSAGE AND ADMINISTRATION

DIRECTIONS: Shake well before use. Children 2-6 years of age: take 1 teaspoon (5mL) every 2 hours, reduce frequency when symptoms improve. Children under 2: consult a physician.

Do not use if cap seal is broken.

INACTIVE INGREDIENT

INACTIVE INGREDIENTS: Acacia Gum, Citric Acid, Glycerin, Grape Flavor, Grape Skin Extract, Potassium Sorbate, Purified Water.

QUESTIONS

Mfg By: OHM PHARMA, INC. Mineral Wells, TX 76067

www.ohmpharma.com

PACKAGE LABEL

HOMEOPATHIC MEDICINE

NDC: 66096-708-25

KIDS COUGH RELIEF SYRUP

Multi - symptom cough relief

Non drowsy - No dyes - No side effects

5 fl oz (148mL) / Alcohol, Gluten, Sugar - Free

PRODUCT OF USA

PURPOSE

Temporarily relieves cough symptoms of diverse origins.